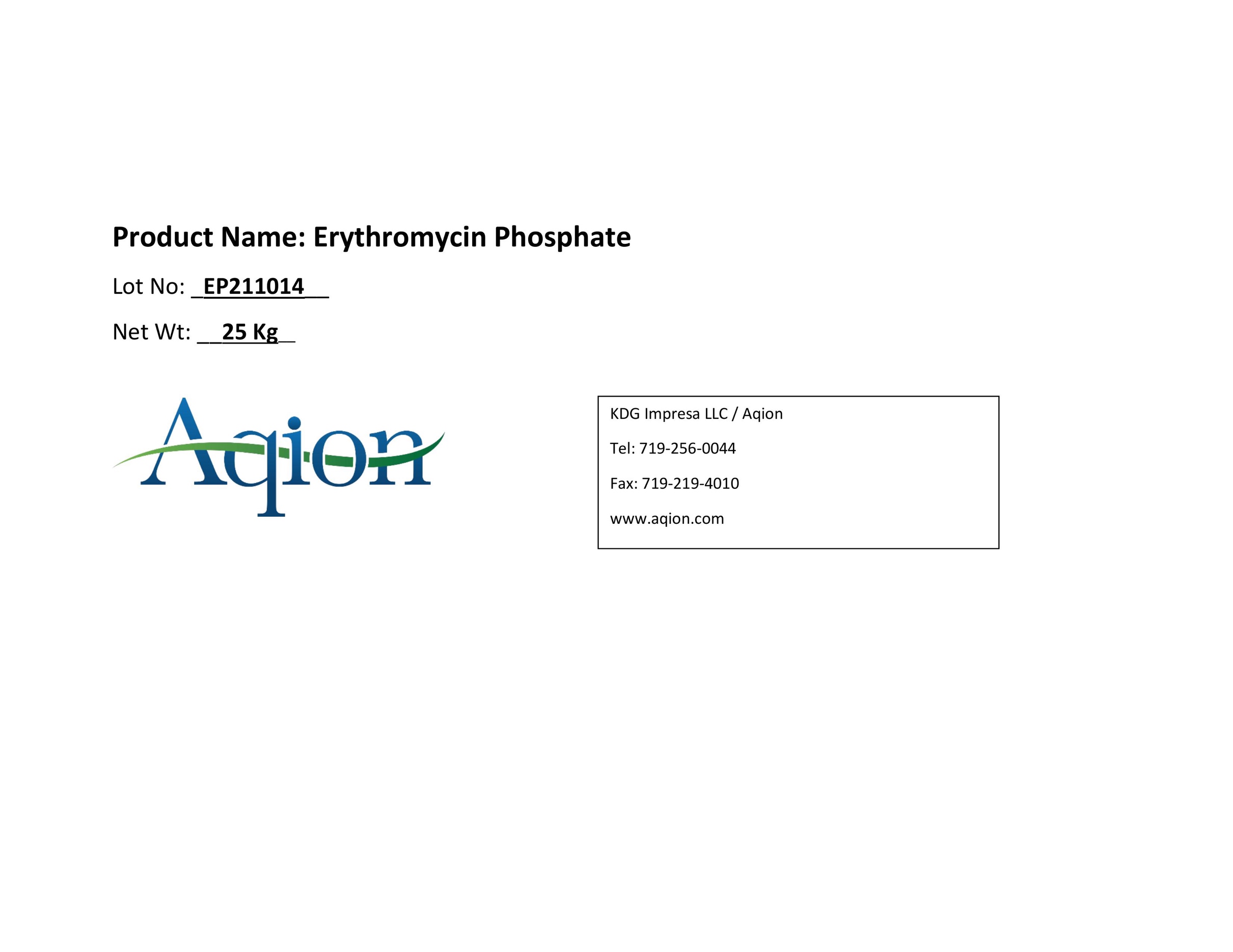 DRUG LABEL: Erythromycin Phosphate
NDC: 43457-543 | Form: POWDER
Manufacturer: KDG Impresa LLC, Aqion
Category: other | Type: BULK INGREDIENT - ANIMAL DRUG
Date: 20220418

ACTIVE INGREDIENTS: Erythromycin Phosphate 1 kg/1 kg

Erythromycin Phosphate